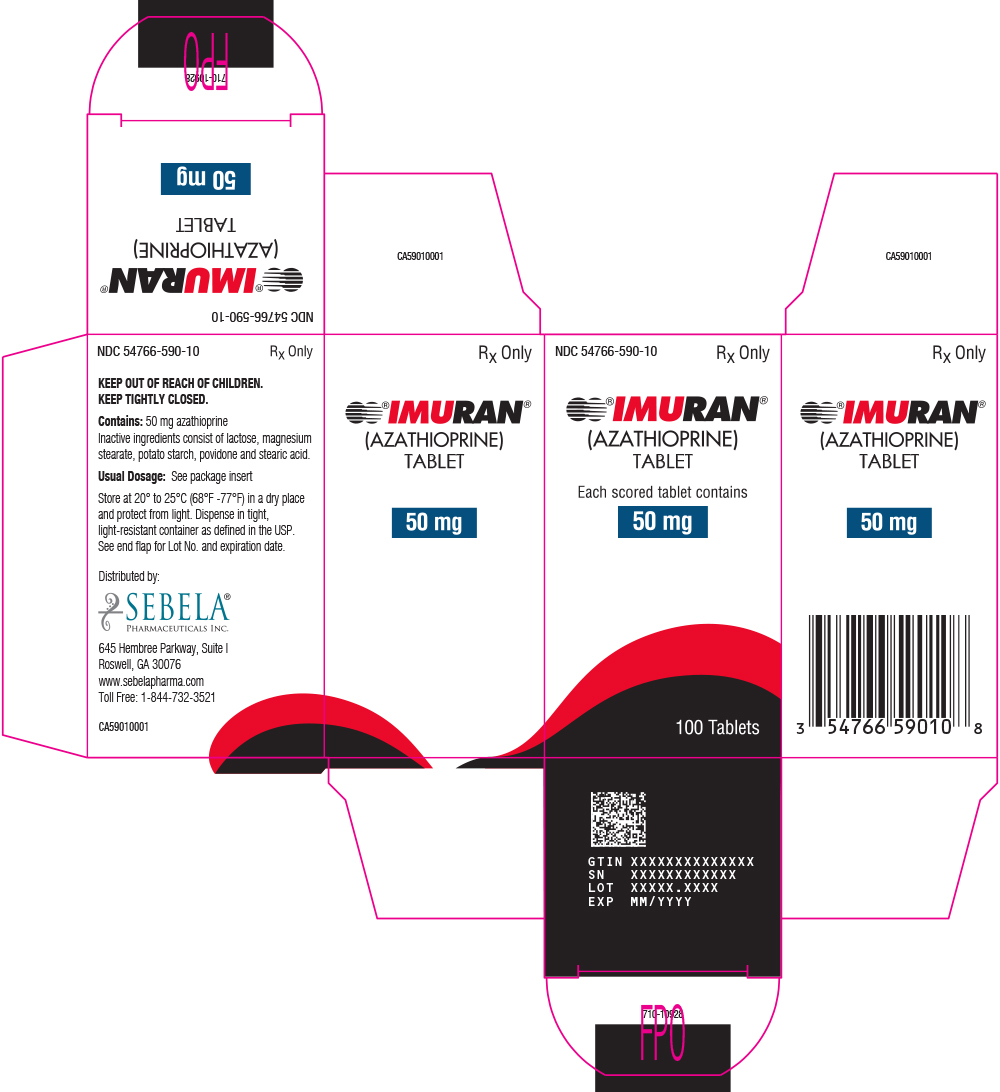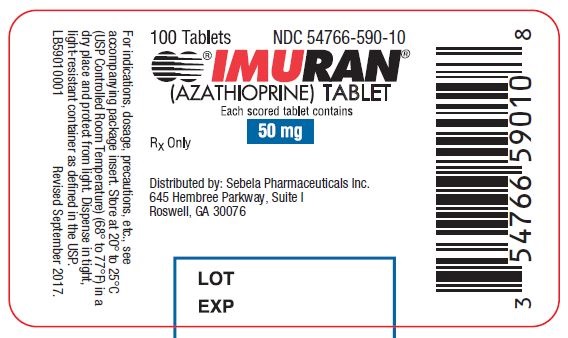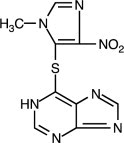 DRUG LABEL: IMURAN
NDC: 54766-590 | Form: TABLET
Manufacturer: Sebela Pharmaceuticals Inc.
Category: prescription | Type: HUMAN PRESCRIPTION DRUG LABEL
Date: 20251108

ACTIVE INGREDIENTS: AZATHIOPRINE 50 mg/1 1
INACTIVE INGREDIENTS: MAGNESIUM STEARATE; LACTOSE; STARCH, POTATO; POVIDONE; STEARIC ACID

IMURAN® (azathioprine)
50-mg Scored Tablets

PRODUCT INFORMATION
Rx only

WARNING - MALIGNANCY

Chronic immunosuppression with IMURAN, a purine antimetabolite increases risk of malignancy in humans. Reports of malignancy include post-transplant lymphoma and hepatosplenic T-cell lymphoma (HSTCL) in patients with inflammatory bowel disease. Physicians using this drug should be very familiar with this risk as well as with the mutagenic potential to both men and women and with possible hematologic toxicities. Physicians should inform patients of the risk of malignancy with IMURAN. See WARNINGS.

DESCRIPTION:

IMURAN (azathioprine), an immunosuppressive antimetabolite, is available in tablet form for oral administration. Each scored tablet contains 50 mg azathioprine and the inactive ingredients lactose, magnesium stearate, potato starch, povidone, and stearic acid.

Azathioprine is chemically 6-[(1-methyl-4-nitro-1 H-imidazol-5-yl)thio]-1 H-purine. The structural formula of azathioprine is:

It is an imidazolyl derivative of 6-mercaptopurine and many of its biological effects are similar to those of the parent compound.

Azathioprine is insoluble in water, but may be dissolved with addition of one molar equivalent of alkali. Azathioprine is stable in solution at neutral or acid pH but hydrolysis to mercaptopurine occurs in excess sodium hydroxide (0.1N), especially on warming. Conversion to mercaptopurine also occurs in the presence of sulfhydryl compounds such as cysteine, glutathione, and hydrogen sulfide.

CLINICAL PHARMACOLOGY:

Azathioprine is well absorbed following oral administration. Maximum serum radioactivity occurs at 1 to 2 hours after oral^35S-azathioprine and decays with a half-life of 5 hours. This is not an estimate of the half-life of azathioprine itself, but is the decay rate for all^35S-containing metabolites of the drug. Because of extensive metabolism, only a fraction of the radioactivity is present as azathioprine. Usual doses produce blood levels of azathioprine, and of mercaptopurine derived from it, which are low (<1 mcg/mL). Blood levels are of little predictive value for therapy since the magnitude and duration of clinical effects correlate with thiopurine nucleotide levels in tissues rather than with plasma drug levels. Azathioprine and mercaptopurine are moderately bound to serum proteins (30%) and are partially dialyzable. See OVERDOSAGE.

Azathioprine is metabolized to 6-mercaptopurine (6-MP). Both compounds are rapidly eliminated from blood and are oxidized or methylated in erythrocytes and liver; no azathioprine or mercaptopurine is detectable in urine after 8 hours. Activation of 6-mercaptopurine occurs via hypoxanthine-guanine phosphoribosyltransferase (HGPRT) and a series of multi-enzymatic processes involving kinases to form 6-thioguanine nucleotides (6-TGNs) as major metabolites). The cytotoxicity of azathioprine is due, in part, to the incorporation of 6-TGN into DNA.

6-MP undergoes two major inactivation routes. One is thiol methylation, which is catalyzed by the enzyme thiopurine S-methyltransferase (TPMT), to form the inactive metabolite methyl-6-MP (6-MeMP). Another inactivation pathway is oxidation, which is catalyzed by xanthine oxidase (XO) to form 6-thiouric acid. The nucleotide diphosphatase (NUDT15) enzyme is involved in conversion of the 6-TGNs to inactive 6-TG monophosphates. TPMT activity correlates inversely with 6-TGN levels in erythrocytes and presumably other hematopoietic tissues, since these cells have negligible xanthine oxidase (involved in the other inactivation pathway) activities.

Genetic polymorphisms influence TPMT and NUDT15 activity. Several published studies indicate that patients with reduced TPMT or NUDT15 activity receiving usual doses of 6-MP or azathioprine, accumulate excessive cellular concentrations of active 6-TGNs, and are at higher risk for severe myelosuppression. Because of the risk of toxicity, patients with TPMT or NUDT15 deficiency require alternative therapy or dose modification (see DOSAGE and ADMINISTRATION).

Approximately 0.3% (1:300) of patients of European or African ancestry have two loss-of-function alleles of the TPMT gene and have little or no TPMT activity (homozygous deficient or poor metabolizers), and approximately 10% of patients have one loss-of-function TPMT allele leading to intermediate TPMT activity (heterozygous deficient or intermediate metabolizers). The TPMT*2, TPMT*3A, and TPMT*3C alleles account for about 95% of individuals with reduced levels of TPMT activity. NUDT15 deficiency is detected in <1% of patients of European or African ancestry. Among patients of East Asian ancestry (i.e., Chinese, Japanese, Vietnamese), 2% have two loss-of-function alleles of the NUDT15 gene, and approximately 21% have one loss-of-function allele. The p.R139C variant of NUDT15 (present on the *2 and *3 alleles) is the most commonly observed, but other less common loss-of-function NUDT15 alleles have been observed.

Inhibition of xanthine oxidase (XO) may cause increased plasma concentrations of azathioprine or its metabolites leading to toxicity (see PRECAUTIONS: Drug Interactions). Proportions of metabolites are different in individual patients, and this presumably accounts for variable magnitude and duration of drug effects. Renal clearance is probably not important in predicting biological effectiveness or toxicities, although dose reduction is practiced in patients with poor renal function.

Homograft Survival: The use of azathioprine for inhibition of renal homograft rejection is well established, the mechanism(s) for this action are somewhat obscure. The drug suppresses hypersensitivities of the cell-mediated type and causes variable alterations in antibody production. Suppression of T-cell effects, including ablation of T-cell suppression, is dependent on the temporal relationship to antigenic stimulus or engraftment. This agent has little effect on established graft rejections or secondary responses.

Alterations in specific immune responses or immunologic functions in transplant recipients are difficult to relate specifically to immunosuppression by azathioprine. These patients have subnormal responses to vaccines, low numbers of T-cells, and abnormal phagocytosis by peripheral blood cells, but their mitogenic responses, serum immunoglobulins, and secondary antibody responses are usually normal.

Immunoinflammatory Response: Azathioprine suppresses disease manifestations as well as underlying pathology in animal models of autoimmune disease. For example, the severity of adjuvant arthritis is reduced by azathioprine.

The mechanisms whereby azathioprine affects autoimmune diseases are not known. Azathioprine is immunosuppressive, delayed hypersensitivity and cellular cytotoxicity tests being suppressed to a greater degree than are antibody responses. In the rat model of adjuvant arthritis, azathioprine has been shown to inhibit the lymph node hyperplasia , which precedes the onset of the signs of the disease. Both the immunosuppressive and therapeutic effects in animal models are dose-related. Azathioprine is considered a slow-acting drug and effects may persist after the drug has been discontinued.

INDICATIONS AND USAGE:

IMURAN is indicated as an adjunct for the prevention of rejection in renal homotransplantation. It is also indicated for the management of active rheumatoid arthritis to reduce signs and symptoms.

Renal Homotransplantation: IMURAN is indicated as an adjunct for the prevention of rejection in renal homotransplantation. Experience with over 16,000 transplants shows a 5-year patient survival of 35% to 55%, but this is dependent on donor, match for HLA antigens, anti-donor or anti-B-cell alloantigen antibody, and other variables. The effect of IMURAN on these variables has not been tested in controlled trials.

Rheumatoid Arthritis: IMURAN is indicated for the treatment of active rheumatoid arthritis (RA) to reduce signs and symptoms. Aspirin, non-steroidal anti-inflammatory drugs and/or low dose glucocorticoids may be continued during treatment with IMURAN. The combined use of IMURAN with disease modifying anti-rheumatic drugs (DMARDs) has not been studied for either added benefit or unexpected adverse effects. The use of IMURAN with these agents cannot be recommended.

CONTRAINDICATIONS:

IMURAN should not be given to patients who have shown hypersensitivity to the drug. IMURAN should not be used for treating rheumatoid arthritis in pregnant women. Patients with rheumatoid arthritis previously treated with alkylating agents (cyclophosphamide, chlorambucil, melphalan, or others) may have a prohibitive risk of malignancy if treated with IMURAN.

WARNINGS:

Malignancy

Patients receiving immunosuppressants, including IMURAN, are at increased risk of developing lymphoma and other malignancies, particularly of the skin. Physicians should inform patients of the risk of malignancy with IMURAN. As usual for patients with increased risk for skin cancer, exposure to sunlight and ultraviolet light should be limited by wearing protective clothing and using a sunscreen with a high protection factor.

Post-transplant

Renal transplant patients are known to have an increased risk of malignancy, predominantly skin cancer and reticulum cell or lymphomatous tumors. The risk of post-transplant lymphomas may be increased in patients who receive aggressive treatment with immunosuppressive drugs, including IMURAN. Therefore, immunosuppressive drug therapy should be maintained at the lowest effective levels.

Rheumatoid Arthritis

Information is available on the risk of malignancy with the use of IMURAN in rheumatoid arthritis (see ADVERSE REACTIONS). It has not been possible to define the precise risk of malignancy due to IMURAN. The data suggest the risk may be elevated in patients with rheumatoid arthritis, though lower than for renal transplant patients. However, acute myelogenous leukemia as well as solid tumors have been reported in patients with rheumatoid arthritis who have received IMURAN.

Inflammatory Bowel Disease

Postmarketing cases of hepatosplenic T-cell lymphoma (HSTCL), a rare type of T-cell lymphoma, have been reported in patients treated with IMURAN. These cases have had a very aggressive disease course and have been fatal. The majority of reported cases have occurred in patients with Crohn's disease or ulcerative colitis and the majority were in adolescent and young adult males. Some of the patients were treated with IMURAN as monotherapy and some had received concomitant treatment with a TNFα blocker at or prior to diagnosis. The safety and efficacy of IMURAN for the treatment of Crohn's disease and ulcerative colitis have not been established.

Cytopenias

Severe leukopenia, thrombocytopenia, anemias including macrocytic anemia, and/or pancytopenia may occur in patients being treated with IMURAN. Severe bone marrow suppression may also occur. Hematologic toxicities are dose-related and may be more severe in renal transplant patients whose homograft is undergoing rejection. It is suggested that patients on IMURAN have complete blood counts, including platelet counts, weekly during the first month, twice monthly for the second and third months of treatment, then monthly or more frequently if dosage alterations or other therapy changes are necessary. Delayed hematologic suppression may occur. Prompt reduction in dosage or temporary withdrawal of the drug may be necessary if there is a rapid fall in or persistently low leukocyte count, or other evidence of bone marrow depression. Leukopenia does not correlate with therapeutic effect; therefore, the dose should not be increased intentionally to lower the white blood cell count.

TPMT or NUDT15 Deficiency

Patients with thiopurine S-methyl transferase (TPMT) or nucleotide diphosphatase (NUDT15) deficiency may be at an increased risk of severe and life-threatening myelotoxicity if receiving conventional doses of IMURAN (see CLINCIAL PHARMACOLOGY). Death associated with pancytopenia has been reported in patients with absent TPMT activity receiving azathioprine. In patients with severe myelosuppression, consider evaluation for TPMT and NUDT15 deficiency (see PRECAUTIONS: Laboratory Tests). Consider alternative therapy in patients with homozygous TPMT or NUDT15 deficiency and reduced dosages in patients with heterozygous deficiency (see DOSAGE AND ADMINISTRATION).

Serious infections

Patients receiving immunosuppressants, including Imuran, are at increased risk for bacterial, viral, fungal, protozoal, and opportunistic infections, including reactivation of latent infections. These infections may lead to serious, including fatal outcomes.

Progressive Multifocal Leukoencephalopathy

Cases of JC virus-associated infection resulting in progressive multifocal leukoencephalopathy (PML), sometimes fatal, have been reported in patients treated with immunosuppressants, including Imuran. Risk factors for PML include treatment with immunosuppressant therapies and impairment of immune function. Consider the diagnosis of PML in any patient presenting with new-onset neurological manifestations and consider consultation with a neurologist as clinically indicated. Consider reducing the amount of immunosuppression in patients who develop PML. In transplant patients, consider the risk that the reduced immunosuppression represents to the graft.

Effect on Sperm in Animals

IMURAN has been reported to cause temporary depression in spermatogenesis and reduction in sperm viability and sperm count in mice at doses 10 times the human therapeutic dose^1; a reduced percentage of fertile matings occurred when animals received 5 mg/kg.^2

IMURAN can cause fetal harm when administered to a pregnant woman. IMURAN should not be given during pregnancy without careful weighing of risk versus benefit. Whenever possible, use of IMURAN in pregnant patients should be avoided. This drug should not be used for treating rheumatoid arthritis in pregnant women.^3

IMURAN is teratogenic in rabbits and mice when given in doses equivalent to the human dose (5 mg/kg daily). Abnormalities included skeletal malformations and visceral anomalies.^2

Postmarketing cases of intrahepatic cholestasis of pregnancy (ICP) have been reported in women treated with azathioprine during pregnancy. ICP symptoms and evaluated bile acid levels improved following azathioprine discontinuation. Discontinue IMURAN if ICP develops in a pregnant woman.

Limited immunologic and other abnormalities have occurred in a few infants born of renal allograft recipients on IMURAN. In a detailed case report,^4 documented lymphopenia, diminished IgG and IgM levels, CMV infection, and a decreased thymic shadow were noted in an infant born to a mother receiving 150 mg azathioprine and 30 mg prednisone daily throughout pregnancy. At 10 weeks most features were normalized. DeWitte et al reported pancytopenia and severe immune deficiency in a preterm infant whose mother received 125 mg azathioprine and 12.5 mg prednisone daily.^5 There have been two published reports of abnormal physical findings. Williamson and Karp described an infant born with preaxial polydactyly whose mother received azathioprine 200 mg daily and prednisone 20 mg every other day during pregnancy.^6 Tallent et al described an infant with a large myelomeningocele in the upper lumbar region, bilateral dislocated hips, and bilateral talipes equinovarus. The father was on long-term azathioprine therapy.^7

Benefit versus risk must be weighed carefully before use of IMURAN in patients of reproductive potential. There are no adequate and well-controlled studies in pregnant women. If this drug is used during pregnancy or if the patient becomes pregnant while taking this drug, the patient should be apprised of the potential hazard to the fetus. Women of childbearing age should be advised to avoid becoming pregnant.

PRECAUTIONS:

GENERAL PRECAUTIONS

General: A gastrointestinal hypersensitivity reaction characterized by severe nausea and vomiting has been reported. These symptoms may also be accompanied by diarrhea, rash, fever, malaise, myalgias, elevations in liver enzymes, and occasionally, hypotension. Symptoms of gastrointestinal toxicity most often develop within the first several weeks of therapy with IMURAN and are reversible upon discontinuation of the drug. The reaction can recur within hours after re-challenge with a single dose of IMURAN.

PATIENT COUNSELING INFORMATION

Information for Patients: Patients being started on IMURAN should be informed of the necessity of periodic blood counts while they are receiving the drug and should be encouraged to report any unusual bleeding or bruising to their physician. They should be informed of the danger of infection while receiving IMURAN and asked to report signs and symptoms of infection to their physician. Careful dosage instructions should be given to the patient, especially when IMURAN is being administered in the presence of impaired renal function or concomitantly with allopurinol (see Drug Interactions subsection and DOSAGE AND ADMINISTRATION). Patients should be advised of the potential risks of the use of IMURAN during pregnancy and during the nursing period. The increased risk of malignancy following therapy with IMURAN should be explained to the patient.

LABORATORY TESTS

Laboratory Tests: Complete Blood Count (CBC) Monitoring: Patients on IMURAN should have complete blood counts, including platelet counts, weekly during the first month, twice monthly for the second and third months of treatment, then monthly or more frequently if dosage alterations or other therapy changes are necessary.

TPMT and NUDT15 Testing: Consider genotyping or phenotyping patients for TPMT deficiency and genotyping for NUDT15 deficiency in patients with severe myelosuppression. TPMT and NUDT15 testing cannot substitute for complete blood count (CBC) monitoring in patients receiving IMURAN. Accurate phenotyping (red blood cell TPMT activity) results are not possible in patients who have received recent blood transfusions (see CLINICAL PHARMACOLOGY, WARNINGS: Cytopenias, ADVERSE REACTIONS and DOSAGE AND ADMINISTRATION sections).

DRUG INTERACTIONS

Drug Interactions: Use with xanthine oxidase (XO) inhibitors: One of the pathways for inactivation of azathioprine is inhibited by XO inhibitors (allopurinol or febuxostat). Patients receiving IMURAN and allopurinol concomitantly should have a dose reduction of IMURAN, to approximately 1/ 3 to 1/ 4 the usual dose. Concomitant use of IMURAN and febuxostat is not recommended. Inhibition of XO may cause increased plasma concentrations of azathioprine or its metabolite, 6-MP, leading to toxicity. It is recommended that a further dose reduction or alternative therapies be considered for patients with low or absent TPMT activity receiving IMURAN and xanthine oxidase inhibitors because both TPMT and XO inactivation pathways are affected (see CLINICAL PHARMACOLOGY, WARNINGS, PRECAUTIONS: Laboratory Tests and ADVERSE REACTIONS sections).

Use with Aminosalicylates: There is in vitro evidence that aminosalicylate derivatives (e.g., sulphasalazine, mesalazine, or olsalazine) inhibit the TPMT enzyme. Concomitant use of these agents with IMURAN should be done with caution.

Use with Other Agents Affecting Myelopoesis: Drugs which may affect leukocyte production, including co-trimoxazole, may lead to exaggerated leukopenia, especially in renal transplant recipients.

Use with Angiotensin-Converting Enzyme Inhibitors: The use of angiotensin-converting enzyme inhibitors to control hypertension in patients on azathioprine has been reported to induce anemia and severe leukopenia.

Use with Warfarin: IMURAN may inhibit the anticoagulant effect of warfarin.

Use with ribavirin: The use of ribavirin for hepatitis C in patients receiving azathioprine has been reported to induce severe pancytopenia and may increase the risk of azathioprine-related myelotoxicity. Inosine monophosphate dehydrogenase (IMDH) is required for one of the metabolic pathways of azathioprine. Ribavirin is known to inhibit IMDH, thereby leading to accumulation of an azathioprine metabolite, 6-methylthioionosine monophosphate (6-MTITP), which is associated with myelotoxicity (neutropenia, thrombocytopenia, and anemia). Patients receiving azathioprine with ribavirin should have complete blood counts, including platelet counts, monitored weekly for the first month, twice monthly for the second and third months of treatment, then monthly or more frequently if dosage or other therapy changes are necessary.

CARCINOGENESIS AND MUTAGENESIS AND IMPAIRMENT OF FERTILITY

Carcinogenesis, Mutagenesis, Impairment of Fertility: See WARNINGS section.

Pregnancy: Teratogenic Effects:See WARNINGS section.

NURSING MOTHERS

Nursing Mothers: The use of IMURAN in nursing mothers is not recommended. Azathioprine or its metabolites are transferred at low levels, both transplacentally and in breast milk.^(8, 9, 10) Because of the potential for tumorigenicity shown for azathioprine, a decision should be made whether to discontinue nursing or discontinue the drug, taking into account the importance of the drug to the mother.

PEDIATRIC USE

Pediatric Use: Safety and efficacy of azathioprine in pediatric patients have not been established.

ADVERSE REACTIONS:

The principal and potentially serious toxic effects of IMURAN are hematologic and gastrointestinal. The risks of secondary infection and malignancy are also significant (see WARNINGS). The frequency and severity of adverse reactions depend on the dose and duration of IMURAN as well as on the patient's underlying disease or concomitant therapies. The incidence of hematologic toxicities and neoplasia encountered in groups of renal homograft recipients is significantly higher than that in studies employing IMURAN for rheumatoid arthritis. The relative incidences in clinical studies are summarized below:

Toxicity | Renal Homograft | Rheumatoid Arthritis
Leukopenia (any degree) | >50% | 28%
<2500 cells/mm^3 | 16% | 5.3%
Infections | 20% | <1%
Neoplasia |  | *
Lymphoma | 0.5%
Others | 2.8%
* Data on the rate and risk of neoplasia among persons with rheumatoid arthritis treated with azathioprine are limited. The incidence of lymphoproliferative disease in patients with RA appears to be significantly higher than that in the general population. In one completed study, the rate of lymphoproliferative disease in RA patients receiving higher than recommended doses of azathioprine (5 mg/kg per day) was 1.8 cases per 1000 patient-years of follow-up, compared with 0.8 cases per 1000 patient-years of follow-up in those not receiving azathioprine. However, the proportion of the increased risk attributable to the azathioprine dosage or to other therapies (i.e., alkylating agents) received by patients treated with azathioprine cannot be determined.

Hematologic: Leukopenia and/or thrombocytopenia are dose-dependent and may occur late in the course of therapy with IMURAN. Dose reduction or temporary withdrawal may result in reversal of these toxicities. Infection may occur as a secondary manifestation of bone marrow suppression or leukopenia, but the incidence of infection in renal homotransplantation is 30 to 60 times that in rheumatoid arthritis. Anemias, including macrocytic anemia, and/or bleeding have been reported.

Patients with low or absent TPMT or NUDT15 activity are at increased risk for severe, life-threatening myelosuppression from IMURAN (see CLINICAL PHARMACOLOGY, WARNINGS: Cytopenias and PRECAUTIONS: Laboratory Tests, DOSAGE AND ADMINISTRATION).

Gastrointestinal: Nausea and vomiting may occur within the first few months of therapy with IMURAN, and occurred in approximately 12% of 676 rheumatoid arthritis patients. The frequency of gastric disturbance often can be reduced by administration of the drug in divided doses and/or after meals. However, in some patients, nausea and vomiting may be severe and may be accompanied by symptoms such as diarrhea, fever, malaise, and myalgias (see PRECAUTIONS). Vomiting with abdominal pain may occur rarely with a hypersensitivity pancreatitis. Hepatotoxicity manifest by elevation of serum alkaline phosphatase, bilirubin, and/or serum transaminases is known to occur following azathioprine use, primarily in allograft recipients. Hepatotoxicity has been uncommon (less than 1%) in rheumatoid arthritis patients. Hepatotoxicity following transplantation most often occurs within 6 months of transplantation and is generally reversible after interruption of IMURAN. A rare, but life-threatening hepatic veno-occlusive disease associated with chronic administration of azathioprine has been described in transplant patients and in one patient receiving IMURAN for panuveitis.^(11, 12, 13) Periodic measurement of serum transaminases, alkaline phosphatase, and bilirubin is indicated for early detection of hepatotoxicity. If hepatic veno-occlusive disease is clinically suspected, IMURAN should be permanently withdrawn.

Others: Additional side effects of low frequency have been reported. These include skin rashes, alopecia, fever, arthralgias, diarrhea, steatorrhea, negative nitrogen balance, reversible interstitial pneumonitis, hepatosplenic T-cell lymphoma (see Warnings – Malignancy), and Sweet's Syndrome (acute febrile neutrophilic dermatosis).

Postmarketing Experience
The following adverse reactions have been identified during postapproval use of IMURAN. Because these reactions are reported voluntarily from a population of uncertain size, it is not always possible to reliably estimate their frequency or establish a casual relationship to drug exposure.

- intrahepatic cholestasis of pregnancy (see WARNINGS, Pregnancy).

OVERDOSAGE:

The oral LD50s for single doses of IMURAN in mice and rats are 2500 mg/kg and 400 mg/kg, respectively. Very large doses of this antimetabolite may lead to marrow hypoplasia, bleeding, infection, and death. About 30% of IMURAN is bound to serum proteins, but approximately 45% is removed during an 8-hour hemodialysis.^14 A single case has been reported of a renal transplant patient who ingested a single dose of 7500 mg IMURAN. The immediate toxic reactions were nausea, vomiting, and diarrhea, followed by mild leukopenia and mild abnormalities in liver function. The white blood cell count, SGOT, and bilirubin returned to normal 6 days after the overdose.

DOSAGE AND ADMINISTRATION:

TPMT TESTING CANNOT SUBSTITUTE FOR COMPLETE BLOOD COUNT (CBC) MONITORING IN PATIENTS RECEIVING IMURAN. TPMT genotyping or phenotyping can be used to identify patients with absent or reduced TPMT activity. Patients with low or absent TPMT activity are at an increased risk of developing severe, life-threatening myelotoxicity from IMURAN if conventional doses are given. Physicians may consider alternative therapies for patients who have low or absent TPMT activity (homozygous for non-functional alleles). IMURAN should be administered with caution to patients having one non-functional allele (heterozygous) who are at risk for reduced TPMT activity that may lead to toxicity if conventional doses are given. Dosage reduction is recommended in patients with reduced TPMT activity. Early drug discontinuation may be considered in patients with abnormal CBC results that do not respond to dose reduction.

Renal Homotransplantation: The dose of IMURAN required to prevent rejection and minimize toxicity will vary with individual patients; this necessitates careful management. The initial dose is usually 3 to 5 mg/kg daily, beginning at the time of transplant. IMURAN is usually given as a single daily dose on the day of, and in a minority of cases 1 to 3 days before, transplantation. Dose reduction to maintenance levels of 1 to 3 mg/kg daily is usually possible. The dose of IMURAN should not be increased to toxic levels because of threatened rejection. Discontinuation may be necessary for severe hematologic or other toxicity, even if rejection of the homograft may be a consequence of drug withdrawal.

Rheumatoid Arthritis: IMURAN is usually given on a daily basis. The initial dose should be approximately 1.0 mg/kg (50 to 100 mg) given as a single dose or on a twice-daily schedule. The dose may be increased, beginning at 6 to 8 weeks and thereafter by steps at 4-week intervals, if there are no serious toxicities and if initial response is unsatisfactory. Dose increments should be 0.5 mg/kg daily, up to a maximum dose of 2.5 mg/kg per day. Therapeutic response occurs after several weeks of treatment, usually 6 to 8; an adequate trial should be a minimum of 12 weeks. Patients not improved after 12 weeks can be considered refractory. IMURAN may be continued long-term in patients with clinical response, but patients should be monitored carefully, and gradual dosage reduction should be attempted to reduce risk of toxicities.

Maintenance therapy should be at the lowest effective dose, and the dose given can be lowered decrementally with changes of 0.5 mg/kg or approximately 25 mg daily every 4 weeks while other therapy is kept constant. The optimum duration of maintenance IMURAN has not been determined. IMURAN can be discontinued abruptly, but delayed effects are possible.

Patients with TPMT and/or NUDT15 Deficiency

Consider testing for TPMT and NUDT15 deficiency in patients who experience severe bone marrow toxicities. Early drug discontinuation may be considered in patients with abnormal CBC results that do not respond to dose reduction (see CLINICAL PHARMACOLOGY, WARNINGS: Cytopenias, and PRECAUTIONS: Laboratory Tests).

Homozygous deficiency in either TPMT or NUDT15

Because of the risk of increased toxicity, consider alternative therapies for patients who are known to have TPMT or NUDT15 deficiency (see CLINICAL PHARMACOLOGY, WARNINGS: Cytopenias, and PRECAUTIONS: Laboratory Tests).

Heterozygous deficiency in TPMT and/or NUDT15

Because of the risk of increased toxicity, dosage reduction is recommended in patients known to have heterozygous deficiency of TPMT or NUDT15. Patients who are heterozygous for both TPMT and NUDT15 deficiency may require more substantial dosage reductions (see CLINICAL PHARMACOLOGY, WARNINGS: Cytopenias, and PRECAUTIONS: Laboratory Tests).

Use in Renal Dysfunction: Relatively oliguric patients, especially those with tubular necrosis in the immediate postcadaveric transplant period, may have delayed clearance of IMURAN or its metabolites, may be particularly sensitive to this drug, and are usually given lower doses.

Procedures for proper handling and disposal of this immunosuppressive antimetabolite drug should be considered. Several guidelines on this subject have been published.^15-21 There is no general agreement that all of the procedures recommended in the guidelines are necessary or appropriate.

HOW SUPPLIED:

50 mg overlapping circle-shaped, yellow to off-white, scored tablets imprinted with “IMURAN” and “50” on each tablet; bottle of 100 (NDC 54766-590-10).

STORAGE AND HANDLING

Store at 20-25 °C (USP Controlled Room Temperature) (68° to 77°F) in a dry place and protect from light.

REFERENCES:

1. Clark JM. The mutagenicity of azathioprine in mice, Drosophila melanogaster, and Neurospora crassa. Mutat Res. 1975; 28:87-99.
2. Data on file, Sebela Ireland Ltd.
3. Tagatz GE, Simmons RL. Pregnancy after renal transplantation. Ann Intern Med. 1975; 82:113-114. Editorial Notes.
4. Cote' CJ, Meuwissen HJ, Pickering RJ. Effects on the neonate of prednisone and azathioprine administered to the mother during pregnancy . J Pediatr. 1974; 85:324-328.
5. DeWitte DB, Buick MK, Cyran SE, et al. Neonatal pancytopenia and severe combined immunodeficiency associated with antenatal administration of azathioprine and prednisone. J Pediatr. 1984; 105:625-628.
6. Williamson RA, Karp LE. Azathioprine teratogenicity: review of the literature and case report. Obstet Gynecol. 1981; 58:247-250.
7. Tallent MB, Simmons RL, Najarian JS. Birth defects in child of male recipient of kidney transplant. JAMA. 1970; 211: 1854-1855.
8. Data on file, Sebela Ireland Ltd.
9. Saarikoski S, Seppälä M. Immunosuppression during pregnancy: transmission of azathioprine and its metabolites from the mother to the fetus. Am J Obstet Gynecol. 1973; 115:1100-1106.
10. Coulam CB, Moyer TP, Jiang NS, et al. Breast-feeding after renal transplantation. Transplant Proc. 1982; 14: 605-609.
11. Read AE, Wiesner RH, LaBrecque DR, et al. Hepatic veno-occlusive disease associated with renal transplantation and azathioprine therapy. Ann Intern Med. 1986; 104:651-655.
12. Katzka DA, Saul SH, Jorkasky D, et al. Azathioprine and hepatic veno-occlusive disease in renal transplant patients. Gastroenterology. 1986; 90:446-454.
13. Weitz H, Gokel JM, Loeshke K, et al. Veno-occlusive disease of the liver in patients receiving immunosuppressive therapy. Virchows Arch A Pathol Anat Histol. 1982; 395:245-256.
14. Schusziarra V, Ziekursch V, Schlamp R, et al. Pharmacokinetics of azathioprine under haemodialysis. Int J Clin Pharmacol Biopharm. 1976; 14:298-302.
15. Recommendations for the safe handling of parenteral antineoplastic drugs. Washington, DC: Division of Safety; Clinical Center Pharmacy Department and Cancer Nursing Services, National Institute of Health; 1992. US Dept of Health and Human Services. Public Health Service Publication NIH 92-2621.
16. AMA Council on Scientific Affairs. Guidelines for handling parenteral antineoplastics. JAMA. 1985; 253:1590-1592.
17. National Study Commission on Cytotoxic Exposure. Recommendations for handling cytotoxic agents. 1987. Available from Louis P. Jeffrey, Chairman, National Study Commission on Cytotoxic Exposure. Massachusetts College of Pharmacy and Allied Health Sciences, 179 Longwood Avenue, Boston, MA 02115.
18. Clinical Oncological Society of Australia. Guidelines and recommendations for safe handling of antineoplastic agents. Med J Aust. 1983; 1:426-428.
19. Jones RB, Frank R, Mass T. Safe handling of chemotherapeutic agents: a report from The Mount Sinai Medical Center. CA Cancer J for Clinicians. 1983; 33:258-263.
20. American Society of Hospital Pharmacists. ASHP technical assistance bulletin on handling cytotoxic and hazardous drugs. Am J Hosp Pharm. 1990; 47:1033-1049.
21. Yodaiken RE, Bennett D. OSHA Work-Practice guidelines for personnel dealing with cytotoxic (antineoplastic) drugs. Am J Hosp Pharm, 1996; 43:1193-1204.

IMURAN is a registered trademark of Sebela International Ltd.

Distributed by Sebela Pharmaceuticals Inc.

645 Hembree Parkway, Suite I

Roswell, GA 30076

www.sebelapharma.com

Toll Free 1-844-732-3521

©2024 Sebela Pharmaceuticals Inc. All rights reserved.
Revised 07/2024

PI59010001

Sebela Pharmaceuticals Inc.

PACKAGE LABEL

100 Tablets

NDC 54766-590-10

IMURAN®
(AZATHIOPRINE)

Each scored tablet contains
50 mg

Rx Only

Sebela Pharmaceuticals Inc.